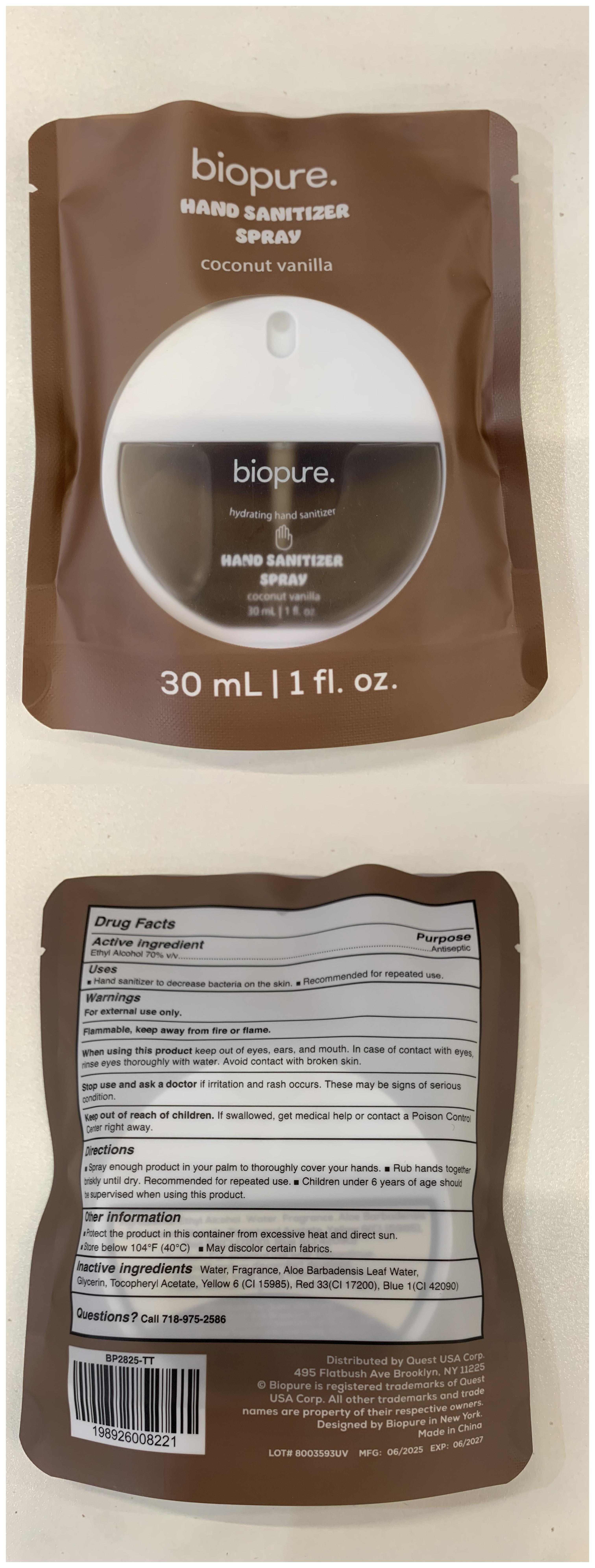 DRUG LABEL: Hand sanitizer
NDC: 77665-106 | Form: SPRAY
Manufacturer: Guangzhou Baihua Co., Ltd
Category: otc | Type: HUMAN OTC DRUG LABEL
Date: 20251214

ACTIVE INGREDIENTS: ALCOHOL 70 g/100 mL
INACTIVE INGREDIENTS: YELLOW 6; WATER; BLUE 1; .ALPHA.-TOCOPHEROL ACETATE; ALOE BARBADENSIS LEAF; RED 33; FRAGRANCE 13576; GLYCERIN

77665-106 Update 003

Active Ingredient

Ethyl Alcohol 70%

Purpose

Antiseptic

Use

Hand sanitizer to decrease bacteria on the skin, Recommended for repeated use.

Warnings

For external use only
Flammable, keep away from fire or flame

Do not use

if irritation and rash occurs. These may be signs of serious condition.

When Using

When using this product keep out of eye, ears, and mouth. In case of contact with eyes, rinse eyes thoroughly with water. Avoid contact with broken skin

Stop Use

Stop use and ask a doctor if irritation and rash occurs. These may be signs of serious condition.

Ask Doctor

Stop use and ask a doctor if irritation and rash occurs. These may be signs of serious condition.

Keep out of reach of children, if swallowed, get medical help or contact a poison control center right away

Directions

Spray enough product in your palm to thoroughly cover your hands, rub hands together briskly until dry, recommended to repeated use, children under 6 years of age should be supervised when using this product

Other information

Protect the product in this container from excessive heat and direct sun.
Store below 104 °F(40 °C)
May discolorcertain fabrics

Inactive ingredients

Water, Fragrance, Aloe Barbadensis Leaf Water,Glycerin, Tocopheryl Acetate, Yellow 6 (Cl 15985), Red 33(Cl 17200), Blue 1(Cl 42090)

Questions

Call 718-975-2586